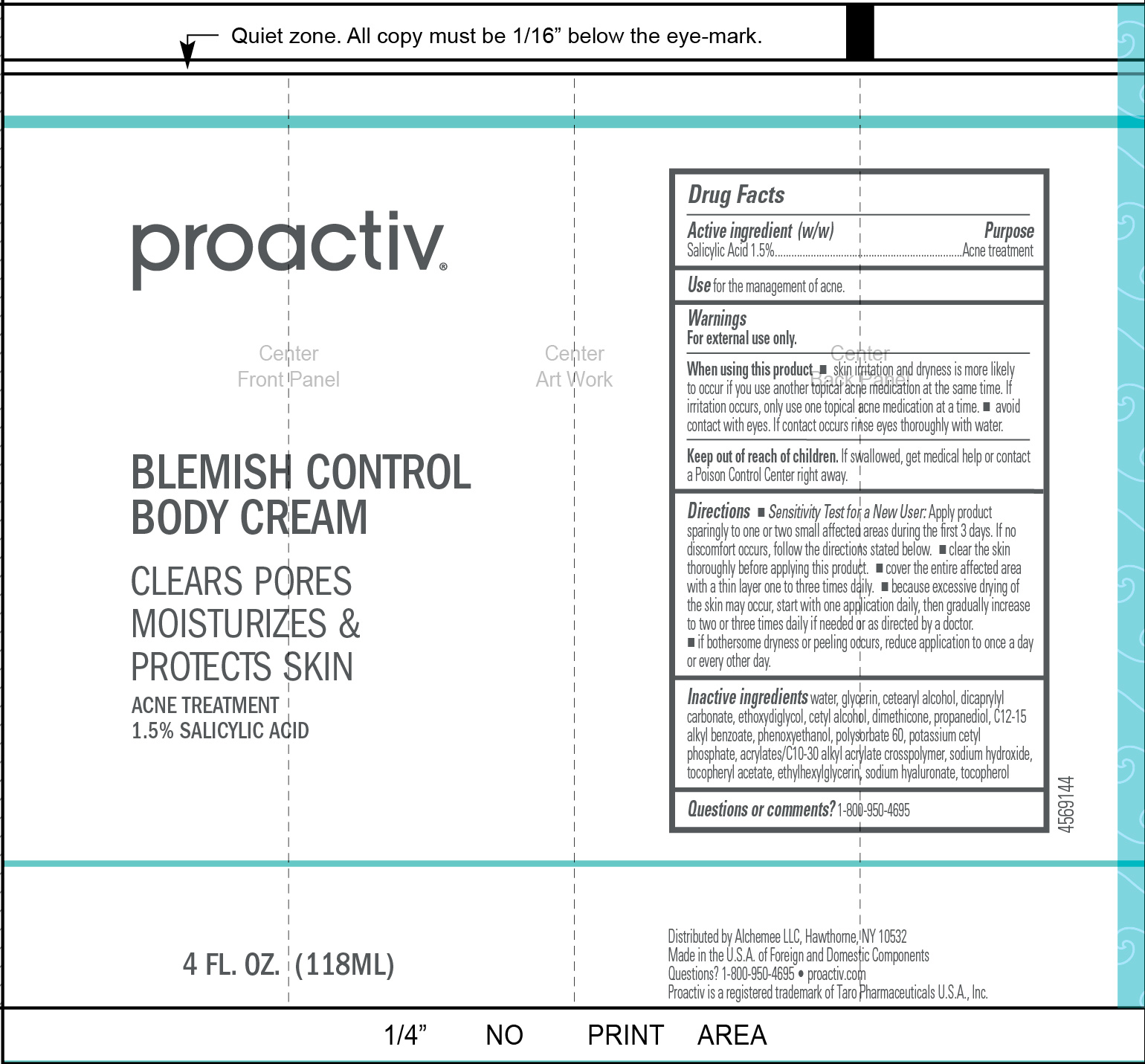 DRUG LABEL: Proactiv Blemish Control Body Cream
NDC: 11410-214 | Form: CREAM
Manufacturer: Alchemee, LLC
Category: otc | Type: HUMAN OTC DRUG LABEL
Date: 20260107

ACTIVE INGREDIENTS: SALICYLIC ACID 15 mg/1 mL
INACTIVE INGREDIENTS: WATER; GLYCERIN; DIMETHICONE; ETHYLHEXYLGLYCERIN; SODIUM HYDROXIDE; PHENOXYETHANOL; PROPANEDIOL; ACRYLATES/C10-30 ALKYL ACRYLATE CROSSPOLYMER (60000 MPA.S); .ALPHA.-TOCOPHEROL ACETATE; POLYSORBATE 60; POTASSIUM CETYL PHOSPHATE; HYALURONATE SODIUM

Proactiv Blemish Control Body Cream

Drug Facts

Active ingredient

Salicylic Acid 1.5%

Purpose

Acne treatment

Use

for the management of acne

Warnings

For external use only

When using this product

- skin irritation and dryness is more likely to occur if you use another topical acne medication at the same time. If irritation occurs, only use one topical acne medication at a time.
- avoid contact with eyes. if contact occurs rinse eyes thoroughly with water.

Keep out of reach of children.

If swallowed, get medical help or contact a Poison Control Center right away.

Directions

- Sensitivity Test for a New User. Apply product sparingly to one or two small affected areas during the first 3 days. If no discomfort occurs, follow the directions stated below.
- clear the skin thoroughly before applying this product.
- cover the entire affected area with a thin layer and rinse thoroughly one to three times daily
- because excessive drying of the skin may occur, start with one application daily, then gradually increase to two or three times daily if needed or as directed by a doctor
- if bothersome dryness or peeling occurs, reduce application to once a day or every other day

Inactive ingredients

Water, Glycerin, Cetearyl Alcohol, Dicaprylyl Carbonate, Ethoxydiglycol, Cetyl Alcohol, Dimethicone, Propanediol, C12-15 Alkyl Benzoate, Phenoxyethanol, Polysorbate 60, Potassium Cetyl Phosphate, Acrylates/C10-30 Alkyl Acrylate Crosspolymer, Sodium Hydroxide, Tocopheryl Acetate, Ethylhexylglycerin, Sodium Hyaluronate, Tocopherol.

Other Information

Store at 20-25°C (68 - 77°F)

Questions or comments?

1-800-950-4695

Distributed by Alchemee LLC, Hawthorne, NY 10532
Made in the USA of Foreign and Domestic Components
Questions? 1-800-950-4695 • proactiv.com • Proactiv is a
registered trademark of Taro Pharmaceuticals U.S.A., Inc.

PRINCIPAL DISPLAY PANEL - 60 mL Carton

proactiv

BLEMISH CONTROL

BODY CREAM
CLEARS PORES

MOISTURIZES &

PROTECTS SKIN

ACNE TREATMENT

1.5% salicylic acid

4 FL. OZ. (118 mL)